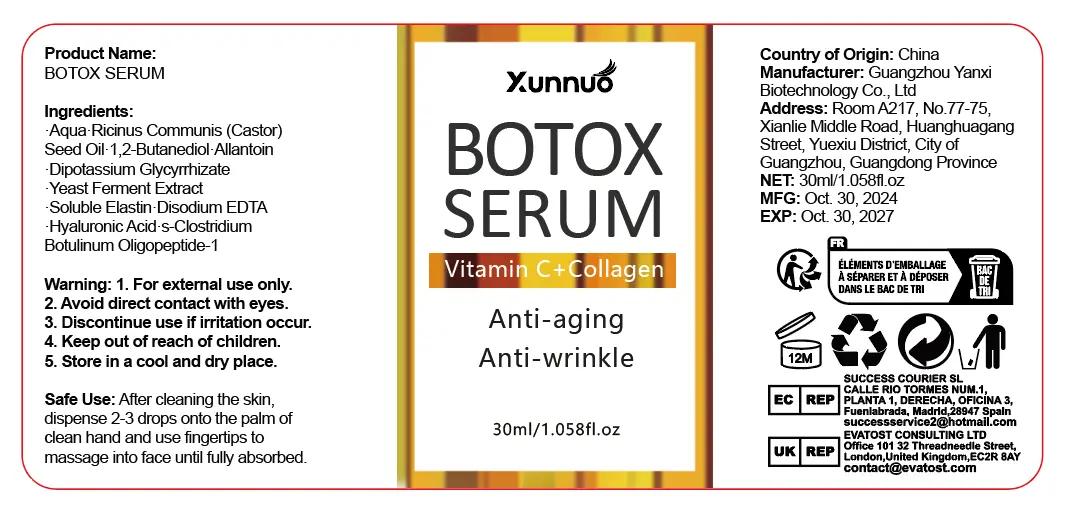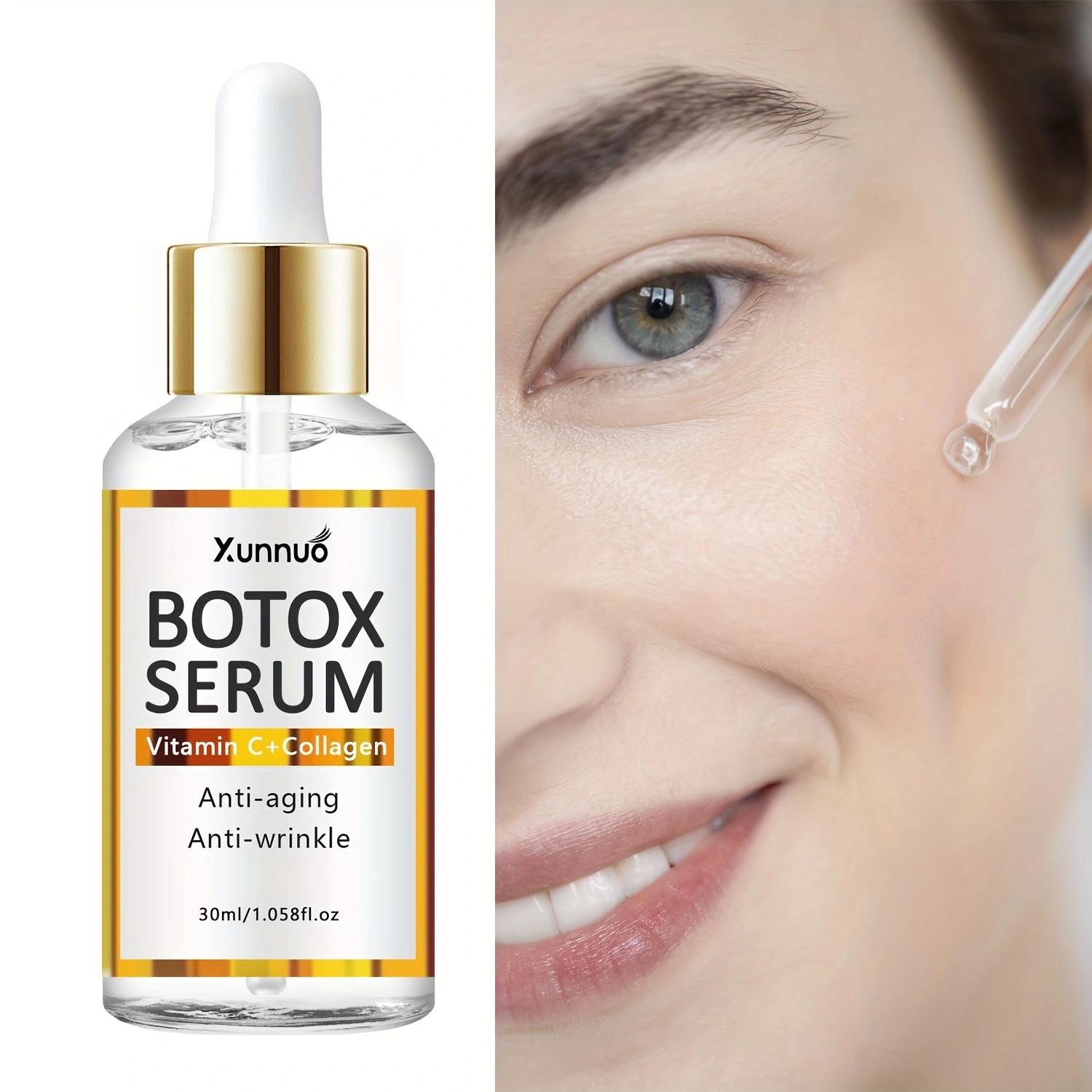 DRUG LABEL: BOTOX SERUM
NDC: 84025-243 | Form: LIQUID
Manufacturer: Guangzhou Yanxi Biotechnology Co., Ltd
Category: otc | Type: HUMAN OTC DRUG LABEL
Date: 20241103

ACTIVE INGREDIENTS: 1,2-BUTANEDIOL 5 mg/100 mL; ALLANTOIN 3 mg/100 mL
INACTIVE INGREDIENTS: WATER

DOSAGE AND ADMINISTRATION

After cleaning the skin, dispense 2-3 drops onto the palm of clean hand and use fingertips to massage into face until fully absorbed.

WARNINGS

keep out of children

INACTIVE INGREDIENT

Aqua

INDICATIONS AND USAGE

for daily face care

keep out of children

PURPOSE

Reduce Fine Lines, Wrinkles, Plump Skin